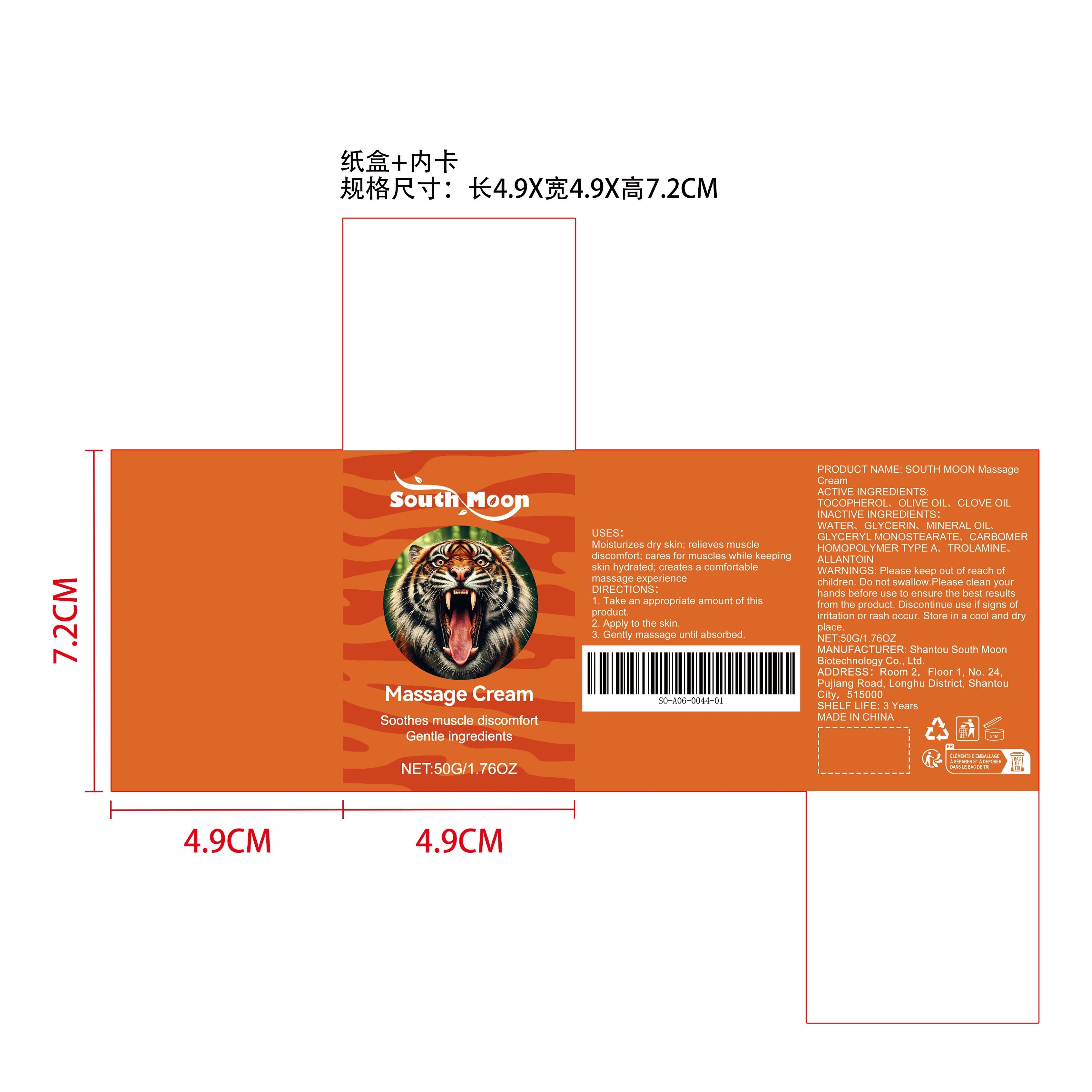 DRUG LABEL: SOUTH MOON Massage Cream
NDC: 84983-016 | Form: CREAM
Manufacturer: Shantou South Moon Biotechnology Co., Ltd.
Category: otc | Type: HUMAN OTC DRUG LABEL
Date: 20251127

ACTIVE INGREDIENTS: OLIVE OIL 0.01 mg/50 mg; CLOVE OIL 0.01 mg/50 mg
INACTIVE INGREDIENTS: GLYCERIN 1.5 mg/50 mg; MINERAL OIL 1.5 mg/50 mg; GLYCERYL MONOSTEARATE 1 mg/50 mg; ALLANTOIN 0.01 mg/50 mg; CARBOMER HOMOPOLYMER TYPE A 0.1 mg/50 mg; TOCOPHEROL 0.01 mg/50 mg; TROLAMINE 0.1 mg/50 mg; WATER 43.26 mg/50 mg

ACTIVE INGREDIENT

OLIVE OIL、CLOVE OIL

PURPOSE

Moisturizes dry skin; relieves muscle discomfort; cares for muscles while keeping skin hydrated; creates a comfortable massage experience

WHEN USING

1. Take an appropriate amount of this product.

2. Apply to the skin.

3. Gently massage until absorbed.

WARNINGS

Please keep out of reach of children. Do not swallow.Please clean your hands before use to ensure the best results from the product. Discontinue use if signs of irritation or rash occur. Store in a cool and dry place.

DO NOT USE

Discontinue use if signs of irritation or rash occur.

STOP USE

Discontinue use if signs of irritation or rash occur.

KEEP OUT OF REACH OF CHILDREN

Please keep out of reach of children. Do not swallow.

STORAGE AND HANDLING

Store in a cool and dry place.

INACTIVE INGREDIENT

TOCOPHEROL、WATER、GLYCERIN、MINERAL OIL、GLYCERYL MONOSTEARATE、CARBOMER HOMOPOLYMER TYPE A、TROLAMINE、ALLANTOIN

DOSAGE AND ADMINISTRATION

1. Take an appropriate amount of this product.

2. Apply to the skin.

3. Gently massage until absorbed.

INDICATIONS AND USAGE

1. Take an appropriate amount of this product.

2. Apply to the skin.

3. Gently massage until absorbed.